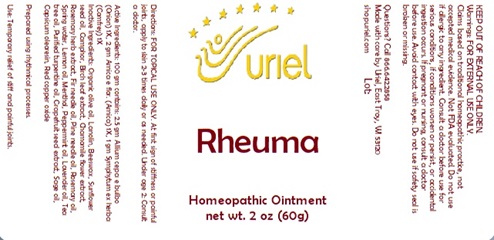 DRUG LABEL: Rheuma
NDC: 48951-8350 | Form: OINTMENT
Manufacturer: Uriel Pharmacy Inc.
Category: homeopathic | Type: HUMAN OTC DRUG LABEL
Date: 20241203

ACTIVE INGREDIENTS: ARNICA MONTANA FLOWER 1 [hp_X]/1 g; COMFREY ROOT 1 [hp_X]/1 g; ONION 1 [hp_X]/1 g
INACTIVE INGREDIENTS: TURPENTINE OIL; TEA TREE OIL; SAGE OIL; CAPSICUM OLEORESIN; PINE NEEDLE OIL (PINUS SYLVESTRIS); ROSEMARY OIL; CITRUS PARADISI SEED; CUPROUS OXIDE; YELLOW WAX; PEPPERMINT OIL; MENTHOL; LEMON OIL; CAMPHOR (NATURAL); BETULA PUBESCENS LEAF; CHAMOMILE; ROSEMARY; LAVENDER OIL; WATER; OLIVE OIL; SUNFLOWER SEED; ABIES SIBIRICA LEAF OIL; LANOLIN

Rheuma

INDICATIONS AND USAGE

Directions: FOR TOPICAL USE ONLY.

DOSAGE AND ADMINISTRATION

At first sign of stiffness or painful joints, apply to skin 2-3 times daily or as needed. Under age 2: Consult a doctor.

ACTIVE INGREDIENT

Active Ingredients: 100 gm contains: 2.5 gm Allium cepa e bulbo (Onion) 1X, 2 gm Arnica e flor. (Arnica) 1X, 1 gm Symphytum ex herba (Comfrey) 1X

INACTIVE INGREDIENT

Inactive Ingredients: Organic olive oil, Lanolin, Beeswax, Sunflower seed oil, Camphor, Birch leaf extract, Chamomile flower extract, Rosemary herb extract, Fir needle oil, Pine needle oil, Rosemary oil, Spring water, Lemon oil, Menthol, Peppermint oil, Lavender oil, Tea tree oil, Purified turpentine oil, Grapefruit seed extract, Sage oil, Capsicum oleoresin, Red copper oxide

Prepared using rhythmical processes.

PURPOSE

Use: Temporary relief of stiff and painful joints.

KEEP OUT OF REACH OF CHILDREN.

Warnings: FOR EXTERNAL USE ONLY.
Claims based on traditional homeopathic practice, not accepted medical evidence. Not FDA evaluated. Do not use if allergic to any ingredient. Consult a doctor before use for serious conditions, if conditions worsen or persist, or accidental ingestion occurs. If pregnant or nursing, consult a doctor before use. Avoid contact with eyes. Do not use if safety seal is broken or missing.

Questions? Call 866.642.2858
Made with care by Uriel, East Troy, WI 53120
shopuriel.com Lot: